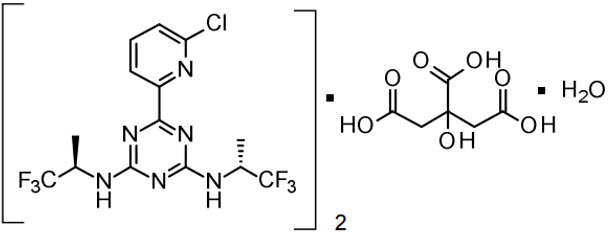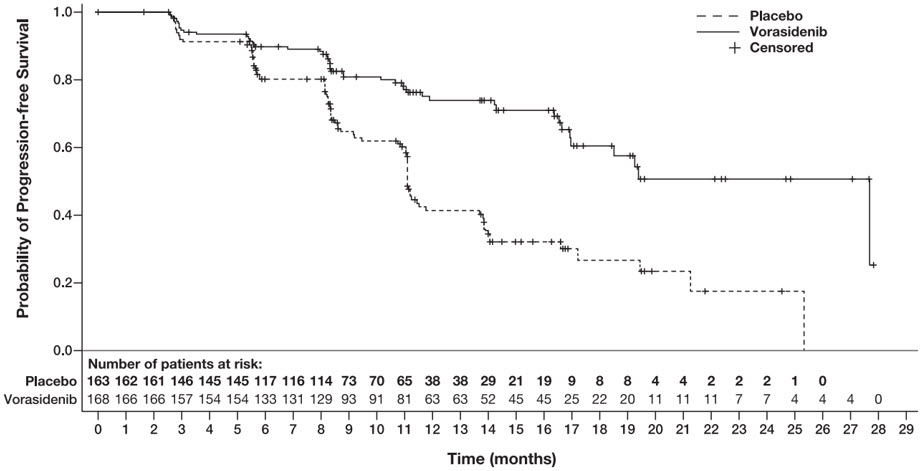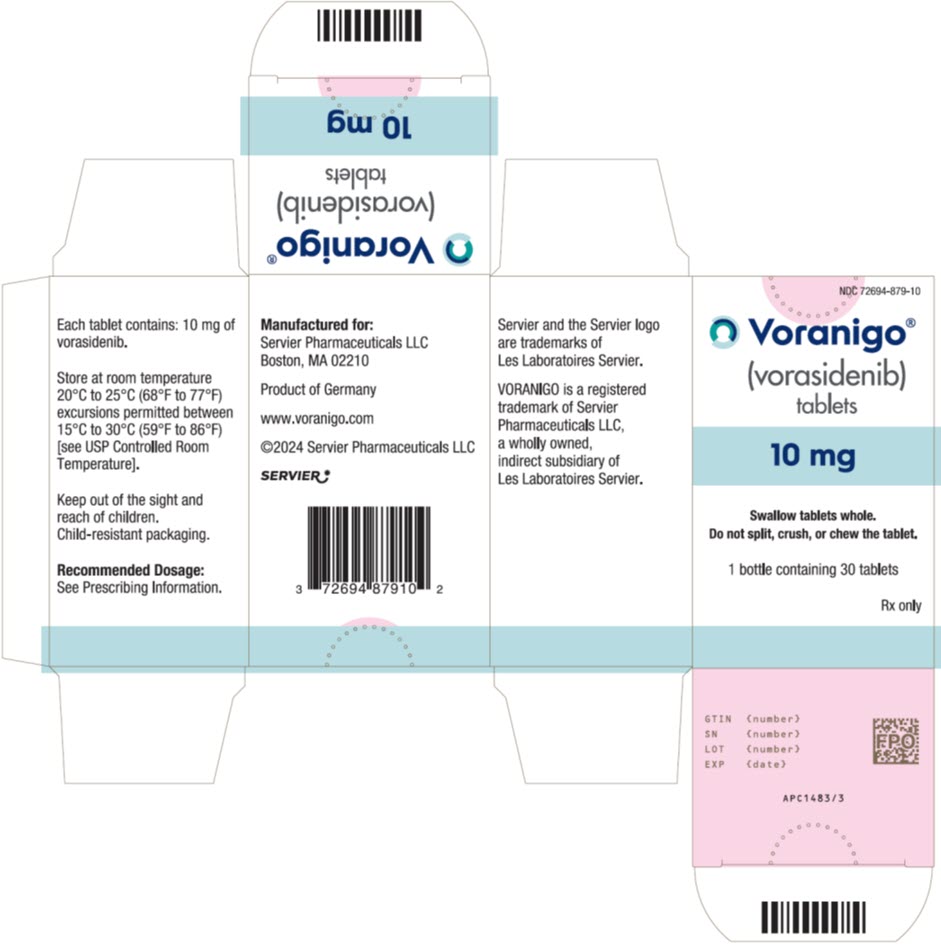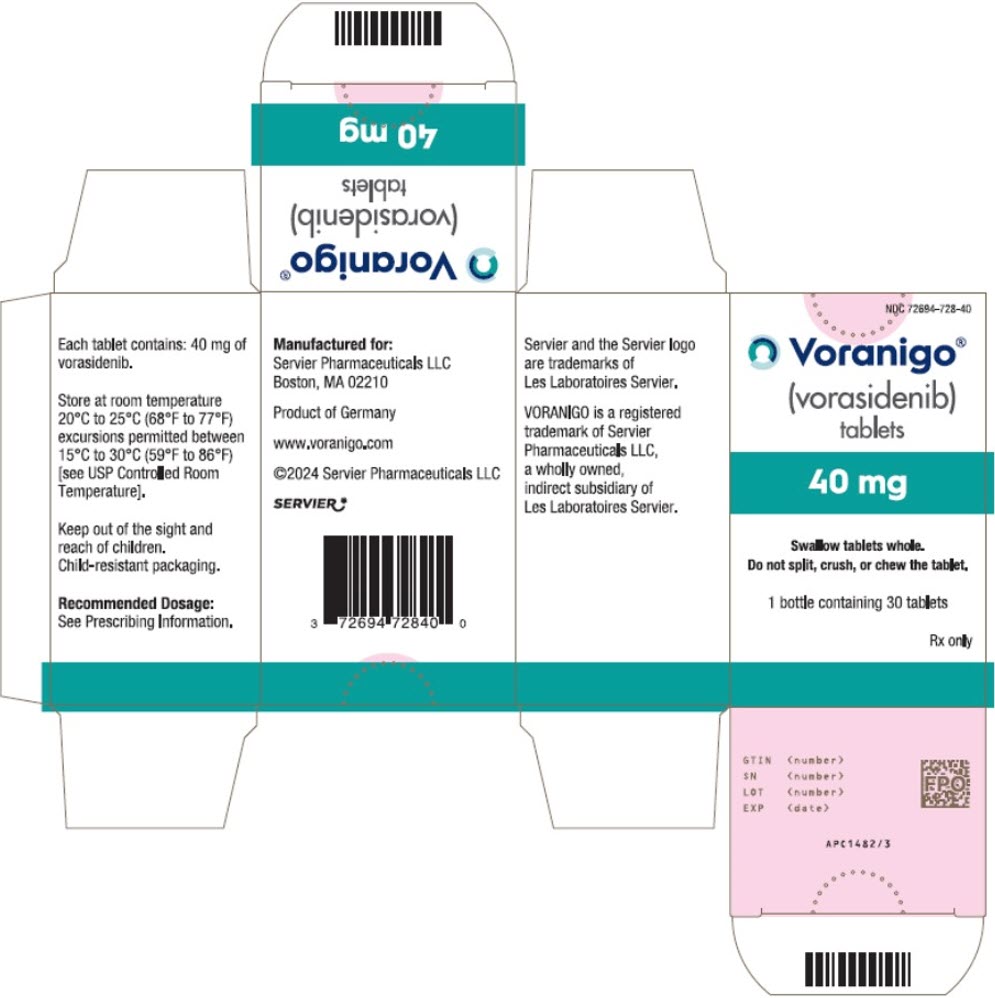 DRUG LABEL: VORANIGO
NDC: 72694-879 | Form: TABLET, FILM COATED
Manufacturer: Servier Pharmaceuticals LLC
Category: prescription | Type: HUMAN PRESCRIPTION DRUG LABEL
Date: 20250408

ACTIVE INGREDIENTS: vorasidenib 10 mg/1 1
INACTIVE INGREDIENTS: microcrystalline cellulose; croscarmellose sodium; silicon dioxide; sodium lauryl sulfate; magnesium stearate; HYPROMELLOSE, UNSPECIFIED; lactose monohydrate; POLYETHYLENE GLYCOL, UNSPECIFIED; titanium dioxide; FERROSOFERRIC OXIDE; propylene glycol

HIGHLIGHTS OF PRESCRIBING INFORMATION

These highlights do not include all the information needed to use VORANIGO safely and effectively. See full prescribing information for VORANIGO.
VORANIGO® (vorasidenib) tablets, for oral use
Initial U.S. Approval: 2024

RECENT MAJOR CHANGES

Indications and Usage (1) | 04/2025
Dosage and Administration, Patient Selection (2.2) | 04/2025

1 INDICATIONS AND USAGE

VORANIGO is an isocitrate dehydrogenase-1 (IDH1) and isocitrate dehydrogenase-2 (IDH2) inhibitor indicated for the treatment of adult and pediatric patients 12 years and older with Grade 2 astrocytoma or oligodendroglioma with a susceptible IDH1 or IDH2 mutation, as detected by an FDA-approved test, following surgery including biopsy, sub-total resection, or gross total resection. (1)

2 DOSAGE AND ADMINISTRATION

- Recommended dosage in adults: (2.3)
  - 40 mg orally once daily
- Recommended dosage in pediatric patients 12 years of age and older based on body weight: (2.3)
  - ≥40 kg: 40 mg orally once daily
  - <40 kg: 20 mg orally once daily
- Take with or without food. (2.3)

3 DOSAGE FORMS AND STRENGTHS

Tablets: 10 mg and 40 mg. (3)

4 CONTRAINDICATIONS

None. (4)

5 WARNINGS AND PRECAUTIONS

- Hepatotoxicity: Monitor liver function tests every 2 weeks during the first 2 months of treatment, then monthly for the first 2 years of treatment, and as clinically indicated. Withhold, reduce the dose or discontinue VORANIGO based on severity. (2.3, 5.1)
- Embryo-Fetal Toxicity: VORANIGO can cause fetal harm. Advise patients of the potential risk to a fetus and to use effective nonhormonal contraception. (5.2, 8.1, 8.3)

6 ADVERSE REACTIONS

The most common (≥15%) adverse reactions include fatigue, headache, COVID-19, musculoskeletal pain, diarrhea, nausea, and seizure.

Grade 3 or 4 (≥2%) laboratory abnormalities were ALT increased, AST increased, GGT increased, and neutrophils decreased. (6.1)

To report SUSPECTED ADVERSE REACTIONS, contact Servier Pharmaceuticals at 1-800-807-6124 or FDA at 1-800-FDA-1088 or www.fda.gov/medwatch.

7 DRUG INTERACTIONS

- CYP1A2 Inhibitors: Avoid concomitant use of strong and moderate CYP1A2 inhibitors. (7.1)
- CYP1A2 Inducers: Avoid concomitant use of moderate CYP1A2 inducers and smoking tobacco. (7.1)
- Certain CYP3A Substrates: Avoid concomitant use with CYP3A substrates, where a minimal concentration change can reduce efficacy. (7.2)
- Hormonal Contraception: If concomitant use cannot be avoided, use with nonhormonal contraception methods. (7.2)

8 USE IN SPECIFIC POPULATIONS

- Lactation: Advise not to breastfeed. (8.2)
- Infertility: May impair fertility in males and females. (8.3)

FULL PRESCRIBING INFORMATION

1 INDICATIONS AND USAGE

VORANIGO is indicated for the treatment of adult and pediatric patients 12 years and older with Grade 2 astrocytoma or oligodendroglioma with a susceptible isocitrate dehydrogenase-1 (IDH1) or isocitrate dehydrogenase-2 (IDH2) mutation, as detected by an FDA-approved test, following surgery including biopsy, sub-total resection, or gross total resection [see Dosage and Administration (2.1), Clinical Pharmacology (12.1) and Clinical Studies (14)].

2 DOSAGE AND ADMINISTRATION

2.1 Recommended Evaluation Before Initiating VORANIGO

Before initiating VORANIGO, evaluate blood chemistry and liver laboratory tests [see Warnings and Precautions (5.1) and Adverse Reactions (6.1)].

2.2 Patient Selection

Select patients with Grade 2 astrocytoma or oligodendroglioma for treatment with VORANIGO based on the presence of IDH1 or IDH2 mutations in tumor specimens [see Clinical Studies (14)].

Information on FDA-approved tests for detection of IDH1 or IDH2 mutations in Grade 2 astrocytoma or oligodendroglioma for selecting patients for treatment with VORANIGO is available at: https://www.fda.gov/CompanionDiagnostics.

2.3 Recommended Dosage and Administration

Recommended Dosage

Adult Patients

The recommended dosage of VORANIGO in adult patients is 40 mg orally once daily until disease progression or unacceptable toxicity.

Pediatric Patients 12 Years and Older

The recommended dosage of VORANIGO in pediatric patients 12 years and older is based on body weight:

- Patients weighing ≥40 kg: 40 mg orally once daily
- Patients weighing <40 kg: 20 mg orally once daily

Continue treatment with VORANIGO until disease progression or unacceptable toxicity.

Administration

Swallow VORANIGO tablets whole with water with or without food [see Clinical Pharmacology (12.3)]. Do not split, crush or chew tablets.

Missed Dose

Take VORANIGO tablets at about the same time each day. If a dose is missed, take the missed dose as soon as possible within 6 hours. If a dose is missed by more than 6 hours, skip the missed dose and take the next dose at the scheduled time.

Vomiting

If vomiting occurs after taking a dose, do not take a replacement dose, and take the next dose at the scheduled time on the following day.

2.4 Dosage Modifications, Management and Monitoring for Adverse Reactions

The recommended VORANIGO dosage reductions for adverse reactions are provided in Table 1.

Table 1: Recommended VORANIGO Dosage Reductions for Adverse Reactions
Dosage Reduction | Recommended Dose and Schedule
Adult patients and Pediatric patients 12 years and older weighing at least 40 kg
First | 20 mg once daily
Second | 10 mg once daily
Pediatric patients 12 years and older weighing less than 40 kg
First | 10 mg once daily
Permanently discontinue VORANIGO in patients unable to tolerate 10 mg once daily.

The recommended management for adverse reactions and VORANIGO dosage modifications for adverse reactions are provided in Table 2.

Table 2: Recommended VORANIGO Dosage Modifications and Management for Adverse Reactions
Adverse Reaction | Severity [Adverse reactions graded by the National Cancer Institute Common Terminology Criteria for Adverse Events (NCI-CTCAE) version 5.0.] | Management and Dosage Modifications
Hepatotoxicity (Elevation of ALT or AST) [see Warnings and Precautions (5.1)] | Grade 1 ALT or AST increase >ULN to 3 × ULN without concurrent total bilirubin >2 × ULN | Continue VORANIGO at current dose. Monitor liver laboratory tests weekly until recovery to <Grade 1.
Hepatotoxicity (Elevation of ALT or AST) [see Warnings and Precautions (5.1)] | Grade 2 ALT or AST >3 to 5 × ULN without concurrent total bilirubin >2 × ULN | First Occurrence: Withhold VORANIGO until recovery to ≤Grade 1 or baseline.; - Recovery in ≤28 days, resume VORANIGO at the same dose. - Recovery in >28 days, resume VORANIGO at reduced dose [see Table 1].; Recurrence: Withhold VORANIGO until recovery to ≤Grade 1 or baseline, and resume VORANIGO at reduced dose [see Table 1].
Hepatotoxicity (Elevation of ALT or AST) [see Warnings and Precautions (5.1)] | Grade 3 ALT or AST >5 to 20 × ULN without concurrent total bilirubin >2 × ULN | First Occurrence: Withhold VORANIGO until recovery to ≤Grade 1 or baseline.; - Recovery in ≤28 days, resume VORANIGO at reduced dose [see Table 1]. - If not recovered in ≤28 days, permanently discontinue VORANIGO.; Recurrence: Permanently discontinue VORANIGO.
Hepatotoxicity (Elevation of ALT or AST) [see Warnings and Precautions (5.1)] | Grade 2 or 3 Any ALT or AST >3 to 20 × ULN with concurrent total bilirubin >2 × ULN | First Occurrence: Withhold VORANIGO until recovery to ≤Grade 1 or baseline.; - Resume VORANIGO at reduced dose [see Table 1].; Recurrence: Permanently discontinue VORANIGO.
Hepatotoxicity (Elevation of ALT or AST) [see Warnings and Precautions (5.1)] | Grade 4 Any ALT or AST >20 × ULN | Permanently discontinue VORANIGO.
Other Adverse Reactions [see Adverse Reactions (6.1)] | Grade 3 | First Occurrence: Withhold VORANIGO until recovery to ≤Grade 1 or baseline.; - Resume VORANIGO at reduced dose [see Table 1].; Recurrence: Permanently discontinue VORANIGO.
Other Adverse Reactions [see Adverse Reactions (6.1)] | Grade 4 | Permanently discontinue VORANIGO.
Abbreviations: ALT = Alanine aminotransferase; AST = Aspartate aminotransferase; ULN = Upper limit of normal

3 DOSAGE FORMS AND STRENGTHS

Tablets:

- 10 mg: White to off-white, round film-coated tablet imprinted with "10" in black ink on one side and plain on the other side. Each tablet contains 10 mg of vorasidenib.
- 40 mg: White to off-white, oblong film-coated tablet imprinted with "40" in black ink on one side and plain on the other side. Each tablet contains 40 mg of vorasidenib.

4 CONTRAINDICATIONS

None.

5 WARNINGS AND PRECAUTIONS

5.1 Hepatotoxicity

VORANIGO can cause hepatic transaminase elevations, which can lead to hepatic failure, hepatic necrosis, and autoimmune hepatitis.

In the pooled safety population [see Adverse Reactions (6.1)], 58% of patients treated with VORANIGO experienced increased ALT and 44% of patients experienced increased AST. Grade 3 or 4 increased ALT or AST occurred in 9% and 4.8% of patients respectively. Among these patients, 4.1% (10/244) had concurrent Grade 3 to 4 ALT or AST elevations. A total of 34% of patients treated with VORANIGO had increased gamma-glutamyl transferase (GGT), of these 2.2% were Grade 3 or 4. Bilirubin increases occurred in 4.8% of patients treated with VORANIGO, with 0.4% Grade 3 or 4. Nine percent of patients treated with VORANIGO had increased alkaline phosphatase, with 0.9% Grade 3 or 4.

Two patients met the laboratory criteria for Hy's Law and had concurrent elevations in ALT or AST >3 times the upper limit of normal and total bilirubin >2 times the upper limit of normal; these events were associated with cases of autoimmune hepatitis and hepatic failure. The median time to first onset of increased ALT or AST was 57 days (range: 1 to 1049).

Permanent discontinuation of VORANIGO was required for 2.9% of patients with ALT elevations, 1.6% of AST elevations, and 0.4% of GGT elevations. Dosage reductions of VORANIGO were required for 7% of patients with ALT elevations, 1.2% of AST elevations, and 0.4% of GGT elevations. Dosage interruptions were required in 14% of patients with ALT elevations, 6% of AST elevations, and 1.6% of GGT elevations.

Monitor liver laboratory tests (AST, ALT, GGT, total bilirubin and alkaline phosphatase) prior to the start of VORANIGO, every 2 weeks during the first 2 months of treatment, then monthly for the first 2 years of treatment, and as clinically indicated, with more frequent testing in patients who develop transaminase elevations.

Reduce the dose, withhold, or permanently discontinue VORANIGO based on severity [see Dosage and Administration (2.3) and Adverse Reactions (6.1)].

5.2 Embryo-Fetal Toxicity

Based on findings from animal studies, VORANIGO can cause fetal harm when administered to a pregnant woman. In animal embryo-fetal development studies, oral administration of vorasidenib to pregnant rats during the period of organogenesis caused embryo-fetal toxicities at doses ≥45 times the human exposure based on the area under the concentration-time curve (AUC) at the highest recommended dose. Oral administration of vorasidenib to pregnant rabbits during the period of organogenesis resulted in embryo-fetal toxicity at doses ≥8 times the human exposure based on the AUC at the highest recommended dose.

Advise pregnant women and females of reproductive potential of the potential risk to a fetus. Advise females of reproductive potential to use effective nonhormonal contraception during treatment with VORANIGO and for 3 months after the last dose, since VORANIGO can render some hormonal contraceptives ineffective [see Drug Interactions (7.2)]. Advise male patients with female partners of reproductive potential to use effective contraception during treatment with VORANIGO and for 3 months after the last dose [see Use in Specific Populations (8.1, 8.3)].

6 ADVERSE REACTIONS

The following clinically significant adverse reactions are described elsewhere in the labeling:

- Hepatotoxicity [see Warnings and Precautions (5.1)]

6.1 Clinical Trials Experience

Because clinical trials are conducted under widely varying conditions, adverse reaction rates observed in the clinical trials of a drug cannot be directly compared to rates in the clinical trials of another drug and may not reflect the rates observed in practice.

Adverse reactions described in the WARNINGS AND PRECAUTIONS reflect exposure to VORANIGO 40 mg orally once daily until disease progression or unacceptable toxicity in the 244 patients with astrocytoma or oligodendroglioma with susceptible IDH1 or IDH2 mutation in trials AG881-C-002 (NCT02481154, n=11), AG120-881-001 (NCT03343197, n=14) and INDIGO (NCT04164901, n=167 randomized patients and n=52 crossover patients). Among the 244 patients who received VORANIGO, 78% were exposed for 6 months or longer and 44% were exposed for greater than one year. In this pooled safety population, the most common (≥15%) adverse reactions were fatigue (33%), headache (28%), COVID-19 (28%), musculoskeletal pain (24%), diarrhea (21%), nausea (20%), and seizure (16%). In this pooled safety population, the most common (≥2%) Grade 3 or 4 laboratory abnormalities were increased ALT (9%), increased AST (4.8%), increased GGT (2.2%), and decreased neutrophils (2.2%).

INDIGO

The safety of VORANIGO was evaluated in 330 patients with Grade 2 astrocytoma or oligodendroglioma with an IDH1 or IDH2 mutation who received at least one dose of either VORANIGO 40 mg daily (N=167) or placebo (N=163) in the INDIGO trial [see Clinical Studies (14)]. Patients received VORANIGO 40 mg orally once daily or placebo orally once daily until disease progression or unacceptable toxicity. Among the 167 patients who were randomized and received VORANIGO, the median duration of exposure to VORANIGO was 12.7 months (range: 1 to 30 months) with 153 patients (92%) exposed to VORANIGO for at least 6 months and 89 (53%) exposed for at least 1 year.

The demographics of patients randomized to VORANIGO were: median age 41 years (range: 21 to 71 years); 60% male, 74% White, 20% race not reported, 3% Asian, and 1.2% Black or African American; and 5% were Hispanic or Latino.

Serious adverse reactions occurred in 7% of patients who received VORANIGO. The most common serious adverse reactions occurring in ≥2% of patients who received VORANIGO includes seizure (3%).

Permanent discontinuation of VORANIGO due to an adverse reaction occurred in 3.6% of patients. Adverse reactions which resulted in permanent discontinuation of VORANIGO in ≥2% of patients included ALT increased (3%).

Dosage interruptions of VORANIGO due to an adverse reaction occurred in 30% of patients. Adverse reactions which required dose interruption in ≥5% of patients included ALT increased (14%), COVID-19 (9%), and AST increased (6%).

Dose reductions of VORANIGO due to an adverse reaction occurred in 11% of patients. Adverse reactions which required dose reduction in ≥5% of patients included ALT increased (8%).

The most common (≥15%) adverse reactions were fatigue (37%), COVID-19 (33%), musculoskeletal pain (26%), diarrhea (25%), and seizure (16%).

Grade 3 or 4 (≥2%) laboratory abnormalities were ALT increased (10%), AST increased (4.8%), GGT increased (3%) and neutrophil decreased (2.4%).

Adverse reactions and select laboratory abnormalities reported in the INDIGO trial are shown in Tables 3 and 4.

Table 3: Adverse Reactions (≥5%) in Patients with Grade 2 IDH1/2 Mutant Glioma Who Received VORANIGO Compared with Placebo in the INDIGO Trial
 | VORANIGO 40 mg daily (n=167) |  | Placebo (n=163)
Adverse Reaction [Adverse reactions are based on NCI CTCAE v5.0.] | All Grades (%) | Grades 3 or 4 (%) | All Grades (%) | Grades 3 or 4 (%)
General Disorders
Fatigue [Grouped term includes asthenia.] | 37 | 0.6 | 36 | 1.2
Infections and Infestations
COVID-19 | 33 | 0 | 29 | 0
Nervous System Disorders
Seizure [Grouped term includes partial seizures, generalized tonic-clonic seizure, epilepsy, clonic convulsion, and simple partial seizures.] | 16 | 4.2 | 15 | 3.7
Musculoskeletal and Connective Tissue Disorders
Musculoskeletal pain [Grouped term includes arthralgia, back pain, non-cardiac chest pain, pain in extremity, myalgia, neck pain, musculoskeletal chest pain, arthritis, and musculoskeletal stiffness.] | 26 | 0 | 25 | 1.8
Gastrointestinal Disorders
Diarrhea [Grouped term includes feces soft and frequent bowel movements.] | 25 | 0.6 | 17 | 0.6
Constipation | 13 | 0 | 12 | 0
Abdominal pain [Grouped term includes abdominal pain upper, abdominal discomfort, abdominal pain lower, abdominal tenderness, and epigastric discomfort.] | 13 | 0 | 12 | 0
Decreased appetite | 9 | 0 | 3.7 | 0

Table 4: Select Laboratory Abnormalities (≥5%) That Worsened from Baseline in Patients with Grade 2 IDH1/2 Mutant Glioma Who Received VORANIGO in the INDIGO Trial
 | VORANIGO 40 mg daily N=167 |  | Placebo N=163
Parameter | All Grades [Based on NCI CTCAE v5.0.] (% [The denominator used to calculate percentages is N, the number of subjects in the Safety Analysis Set within each treatment group.]) | Grades 3 or 4 (%) | All Grades (%) | Grades 3 or 4 (%)
Chemistry
Increased ALT | 59 | 10 | 25 | 0
Increased AST | 46 | 4.8 | 20 | 0
Increased Creatinine | 11 | 0.6 | 7 | 0
Decreased Calcium | 10 | 0 | 7 | 0
Increased Glucose [Includes adverse reaction term hyperglycemia.] | 10 | 0 | 4.3 | 0
Increased GGT | 38 | 3 | 10 | 1.8
Decreased Phosphate [Includes adverse reaction terms hypophosphatemia and blood phosphorus decreased.] | 8 | 0.6 | 4.9 | 0
Increased Potassium | 23 | 0.6 | 20 | 0
Increased ALP | 10 | 1.2 | 7 | 0.6
Hematology
Increased Hemoglobin | 13 | 0 | 3.1 | 0
Decreased Lymphocytes | 11 | 1.8 | 8 | 0.6
Decreased Leukocytes | 13 | 0.6 | 12 | 0.6
Decreased Neutrophils | 14 | 2.4 | 12 | 1.8
Decreased Platelets | 12 | 0 | 4.3 | 0
Abbreviations: AST = Aspartate Aminotransferase; ALT = Alanine Aminotransferase; GGT = Gamma-Glutamyl Transferase; ALP = Alkaline Phosphatase

7 DRUG INTERACTIONS

7.1 Effect of Other Drugs on VORANIGO

Table 5: Effect of Other Drugs on VORANIGO
Strong and Moderate CYP1A2 Inhibitors
Clinical Impact | - Concomitant use of VORANIGO with a strong or moderate CYP1A2 inhibitor may increase vorasidenib plasma concentrations [see Clinical Pharmacology (12.3)], which may increase the risk of adverse reactions.
Prevention or Management | - Avoid concomitant use of VORANIGO with strong and moderate CYP1A2 inhibitors. - If concomitant use of moderate CYP1A2 inhibitors cannot be avoided, monitor for increased adverse reactions and modify the dosage for adverse reactions as recommended [see Dosage and Administration (2.4)].
Moderate CYP1A2 Inducers
Clinical Impact | - Concomitant use of VORANIGO with moderate CYP1A2 inducers and smoking tobacco may decrease vorasidenib plasma concentrations [see Clinical Pharmacology (12.3)], which may reduce the anti-tumor activity of VORANIGO.
Prevention or Management | - Avoid concomitant use of VORANIGO with moderate CYP1A2 inducers and smoking tobacco.

7.2 Effect of VORANIGO on Other Drugs

Table 6: Effect of VORANIGO on Other Drugs
Certain CYP3A Substrates
Clinical Impact | - Concomitant use of VORANIGO with CYP3A substrates may decrease plasma concentrations of CYP3A substrates.
Prevention or Management | - Avoid concomitant use of VORANIGO with CYP3A substrates, where a minimal concentration change may lead to reduced therapeutic effect.
Hormonal Contraception
Clinical Impact | - Concomitant use of VORANIGO may decrease the concentrations of hormonal contraceptives, which may lead to contraception failure and/or an increase in breakthrough bleeding.
Prevention or Management | - If concomitant use cannot be avoided, use with nonhormonal contraception methods.

8 USE IN SPECIFIC POPULATIONS

8.1 Pregnancy

Risk Summary

Based on findings from animal studies and its mechanism of action [see Clinical Pharmacology (12.1)], VORANIGO can cause fetal harm when administered to a pregnant woman. There are no available data on VORANIGO use in pregnant women to inform a drug-associated risk. In animal embryo-fetal development studies, oral administration of vorasidenib to pregnant rats and rabbits during the period of organogenesis caused embryo-fetal toxicity at ≥8 times the human exposure based on the AUC at the highest recommended dose (see Data). Advise pregnant women of the potential risk to the fetus.

In the U.S. general population, the estimated background risk of major birth defects and miscarriage in clinically recognized pregnancies is 2% to 4% and 15% to 20%, respectively.

Data

Animal Data

In an embryo-fetal development study, vorasidenib was administered to pregnant rats via oral gavage at dose levels of 10, 25, and 75 mg/kg/day during the period of organogenesis (gestation days 6 to 17). Embryo-fetal toxicity (higher incidence of early resorptions, and visceral malformations of kidney and testes) occurred in rats at the maternally toxic dose of 75 mg/kg/day (approximately 170 times the human exposure based on the AUC at the highest recommended dose). Malformation of heart occurred in a rat at a dose of 25 mg/kg (approximately 97 times the human exposure based on the AUC at the highest recommended dose). Dose-related delayed ossification of bones and short ribs associated with decreased fetal body weights was observed at 10 and 25 mg/kg/day in the absence of maternal toxicity and at 75 mg/kg/day. The dose of 10 mg/kg/day is ≥45 times the human exposure based on the AUC at the highest recommended dose.

In an embryo-fetal development study, oral administration of vorasidenib to pregnant rabbits at dose levels of 2, 6, and 18 mg/kg/day during the period of organogenesis (gestation days 6 to 19) resulted in maternal toxicity at all doses (≥1.5 times the human exposure based on the AUC at the highest recommended dose) and caused higher incidence of late resorptions at 18 mg/kg/day as well as decreased fetal weights and delayed ossification at doses ≥6 mg/kg/day (≥8 times the human exposure based on the AUC at the highest recommended dose).

8.2 Lactation

Risk Summary

There are no data on the presence of vorasidenib or its metabolites in human milk, their effects on the breastfed child, or on milk production. Because of the potential for adverse reactions in breastfed children from VORANIGO, advise women not to breastfeed during treatment with VORANIGO and for 2 months after the last dose.

8.3 Females and Males of Reproductive Potential

Based on animal embryo-fetal toxicity studies, VORANIGO can cause fetal harm when administered to pregnant women [see Use in Specific Populations (8.1)].

Pregnancy Testing

Verify pregnancy status in females of reproductive potential prior to starting VORANIGO [see Use in Specific Populations (8.1)].

Contraception

Females

Advise females of reproductive potential to use effective nonhormonal contraception during treatment with VORANIGO and for 3 months after the last dose. VORANIGO can render some hormonal contraceptives ineffective [see Drug Interactions (7.2)].

Males

Advise male patients with female partners of reproductive potential to use effective contraception during treatment with VORANIGO and for 3 months after the last dose.

Infertility

Based on findings in animals, VORANIGO may impair fertility in females and males of reproductive potential. The effects on female and male fertility were not reversible in rats [see Nonclinical Toxicology (13.1)].

8.4 Pediatric Use

The safety and effectiveness of VORANIGO have been established in pediatric patients aged 12 years and older for the treatment of Grade 2 IDH1- or IDH2-mutant astrocytoma or oligodendroglioma. Use of VORANIGO for this indication in this age group is supported by evidence from an adequate and well-controlled study of VORANIGO in adult and pediatric patients with additional population pharmacokinetic data demonstrating that age had no clinically meaningful effect on the pharmacokinetics of vorasidenib. In addition, the course of IDH1- or IDH2-mutant astrocytoma or oligodendroglioma is sufficiently similar between adults and pediatric patients to allow extrapolation of pharmacokinetic data in adults to pediatric patients [see Adverse Reactions (6.1), Clinical Pharmacology (12.3) and Clinical Studies (14)].

The exposure of vorasidenib in pediatric patients 12 years and older is predicted to be within range of exposure observed in adults at the recommended dosages [see Clinical Pharmacology (12.3)].

The safety and effectiveness of VORANIGO have not been established in pediatric patients younger than 12 years of age for any indication.

8.5 Geriatric Use

Of the 167 patients who were randomized and received VORANIGO 40 mg once daily in the INDIGO trial, 1.2% (2 patients) were 65 years or older. Clinical studies of VORANIGO did not include sufficient numbers of patients aged ≥65 to determine whether they respond differently from younger subjects.

8.6 Renal Impairment

No dosage adjustment is recommended for patients with creatinine clearance (CLcr) >40 mL/min.

The pharmacokinetics and safety of vorasidenib in patients with CLcr ≤40 mL/min or renal impairment requiring dialysis have not been studied [see Clinical Pharmacology (12.3)]. For patients with CLcr ≤40 mL/min or who require dialysis, monitor for increased adverse reactions and modify the dosage for adverse reactions as recommended [see Dosage and Administration (2.4), Clinical Pharmacology (12.3)].

8.7 Hepatic Impairment

No dosage adjustment is recommended for patients with mild or moderate (Child-Pugh Class A or B) hepatic impairment [see Clinical Pharmacology (12.3)].

The pharmacokinetics and safety of vorasidenib in patients with severe hepatic impairment (Child-Pugh Class C) have not been studied. For patients with severe hepatic impairment, monitor for increased adverse reactions and modify the dosage for adverse reactions as recommended [see Dosage and Administration (2.4), Clinical Pharmacology (12.3)].

11 DESCRIPTION

VORANIGO tablets contain vorasidenib, an isocitrate dehydrogenase-1 (IDH1) and isocitrate dehydrogenase-2 (IDH2) inhibitor. Vorasidenib is present as the hemicitric acid hemihydrate co-crystal. The chemical name of the co-crystal is 6-(6-chloropyridin-2-yl)-N^2,N^4-bis[(2R)-1,1,1-trifluoropropan-2-yl]-1,3,5-triazine-2,4-diamine, 2-hydroxypropane-1,2,3-tricarboxylic acid, hydrate (2:1:1). It has the following chemical structure:

The molecular formula is C14H13ClF6N6 • ½ C6H8O7• ½ H2O and the molecular weight is 519.8 g/mol. Vorasidenib hemicitric acid hemihydrate is a white to off-white solid practically insoluble in aqueous solutions between pH 1.2 to 6.8.

VORANIGO is available as a 10 mg and 40 mg strength film-coated tablet for oral administration. The strengths reflect the amount of active ingredient vorasidenib in each tablet. Each tablet core contains the following inactive ingredients: croscarmellose sodium, magnesium stearate, microcrystalline cellulose, silicified microcrystalline cellulose and sodium lauryl sulfate. The tablet coating includes hypromellose, lactose monohydrate, macrogol and titanium dioxide. Each tablet is printed with black ink that contains black iron oxide, hypromellose and propylene glycol.

12 CLINICAL PHARMACOLOGY

12.1 Mechanism of Action

Vorasidenib is a small molecule inhibitor that targets isocitrate dehydrogenase-1 and 2 (IDH1 and IDH2) enzymes. In vitro, vorasidenib inhibited the IDH1 wild type and mutant variants, including R132H and the IDH2 wild type and mutant variants. In cell-based and in vivo tumor models expressing IDH1 or IDH2 mutated proteins, vorasidenib decreased production of 2-hydroxyglutarate (2-HG) and partially restored cellular differentiation.

12.2 Pharmacodynamics

Exposure-Response Relationships

Vorasidenib decreases 2-HG tumor concentrations in patients with IDH1 or IDH2 mutated glioma. Relative to tumors from patients in the untreated group, the posterior median percentage reduction (95% credible interval) in tumor 2-HG was 64% (22%, 88%) to 93% (76%, 98%) in tumors from patients who received vorasidenib at exposures that were 0.3 to 0.8 times the exposure observed with the highest recommended dosage.

The exposure-response relationship and time course of pharmacodynamic response for the safety and effectiveness of vorasidenib have not been fully characterized.

Cardiac Electrophysiology

When the recommended dose of VORANIGO is administered 1 hour prior to a meal, a mean increase in the QTc interval >20 msec is unlikely. There is insufficient information to characterize the QTc effects of VORANIGO at higher vorasidenib concentrations, e.g., when administered with a meal or when co-administered with a moderate CYP1A2 inhibitor [see Clinical Pharmacology (12.3)].

12.3 Pharmacokinetics

Vorasidenib maximum plasma concentration (Cmax) and AUC increased approximately proportionally over the dose range of 10 to 200 mg (0.2 to 4 times the exposure of the highest approved recommended dosage) following once daily administration of single and multiple doses. At the highest approved recommended dosage, steady state mean (CV%) Cmax is 133 ng/mL (73%) and AUC is 1,988 h•ng/mL (95%). Steady state is achieved within 28 days of once daily dosing and the mean accumulation ratio of AUC is 4.4.

Absorption

The median (minimum, maximum) time to maximum plasma concentrations (tmax) at steady state is 2 hours (0.5 to 4 hours).

The mean absolute bioavailability of vorasidenib is 34%.

Food Effect

A high-fat and high-calorie (total 800-1,000 calories, of which 500-600 from fat) meal increased vorasidenib Cmax 3.1-fold and AUC 1.4-fold, compared to the fasting conditions.

A low-fat and low-calorie (total 400-500 calories, of which 100-125 from fat) meal increased vorasidenib Cmax 2.3-fold and AUC 1.4-fold, compared to the fasting conditions.

Distribution

The mean (CV%) volume of distribution at steady state of vorasidenib is 3,930 L (40%).

The protein binding is 97% in human plasma independent of vorasidenib concentrations in vitro.

The brain tumor-to-plasma concentration ratio is 1.6.

Elimination

The mean (CV%) steady state terminal half-life is 10 days (57%) and oral clearance is 14 L/h (56%).

Metabolism

Vorasidenib is primarily metabolized by CYP1A2 with minor contributions from CYP2B6, CYP2C8, CYP2C9, CYP2C19, CYP2D6 and CYP3A. Non-CYP pathways may contribute up to 30% of its metabolism.

Excretion

Following a single oral radiolabeled dose of vorasidenib, 85% of the dose was recovered in feces (56% unchanged) and 4.5% was recovered in urine.

Specific Populations

No clinically significant effects on the pharmacokinetics of vorasidenib were observed based on age (16 to 75 years), sex, race (White, Black or African American, Asian, American Indian/Alaskan Native, Native Hawaiian or Other Pacific Islander), ethnicity (Hispanic and non-Hispanic), body weight (43.5 to 168 kg), mild or moderate hepatic impairment (Child-Pugh Class A or B) or CLcr >40 mL/min (as Cockcroft-Gault). The pharmacokinetics of vorasidenib has not been studied in patients with severe hepatic impairment (Child-Pugh Class C), in patients with CLcr ≤40 mL/min or in patients with renal impairment who require dialysis.

Pediatric Patients

The exposure of vorasidenib in pediatric patients ≥12 years of age is predicted to be within range of that observed in adults at the approved recommended dosage.

Drug Interaction Studies

Clinical Studies and Model-Informed Approaches

Effect of Other Drugs on Vorasidenib

Strong and Moderate CYP1A2 Inhibitors: Concomitant use of ciprofloxacin (moderate CYP1A2 inhibitor) increased vorasidenib plasma Cmax 1.3-fold and AUC 2.5-fold.

Concomitant use with fluvoxamine (strong CYP1A2 inhibitor) is predicted to increase vorasidenib Cmax and AUC by ≥5-fold.

Moderate CYP1A2 Inducers: Concomitant use with phenytoin or rifampicin (moderate CYP1A2 inducers) is predicted to decrease vorasidenib steady-state Cmax by 30% and AUC by 40%.

Gastric Acid Reducing Agents: No clinically significant difference in vorasidenib pharmacokinetics was observed following concomitant use with omeprazole (an acid-reducing agent).

Effect of Vorasidenib on Other Drugs

CYP3A Substrates: Concomitant use of multiple doses of vorasidenib with CYP3A substrates is predicted to decrease the concentrations of these substrates.

UGT1A4 Substrate: No clinically significant difference in lamotrigine pharmacokinetics was observed following the administration of lamotrigine with multiple doses of vorasidenib.

P-gp and BCRP Substrates: No clinically significant difference in the pharmacokinetics of digoxin (P-gp substrate) or rosuvastatin (BCRP substrate) is predicted when used concomitantly with vorasidenib.

In vitro Studies

Vorasidenib is an inducer of CYP2B6, CYP2C8, CYP2C9, CYP2C19 and CYP3A and UGT1A4.

Vorasidenib is not a substrate of P-gp, BCRP, or OATP1B1 and OATP1B3.

Vorasidenib is an inhibitor of BCRP. Vorasidenib does not inhibit P-gp and OATP1B1.

13 NONCLINICAL TOXICOLOGY

13.1 Carcinogenesis, Mutagenesis, Impairment of Fertility

Carcinogenicity studies have not been conducted with vorasidenib. Vorasidenib and its major circulating metabolite, AGI-69460, were not mutagenic in an in vitro bacterial reverse mutation (Ames) assay. Vorasidenib was not clastogenic in an in vitro human lymphocyte micronucleus assay, or an in vivo rat bone marrow micronucleus assay.

Fertility studies in animals have not been conducted with vorasidenib. In repeat-dose toxicity studies up to 13 weeks in duration with oral administration of vorasidenib in rats, adverse effects in female reproductive organs included atrophy, decreased/absent corpora lutea, increased atretic follicles, and interstitial cell vacuolation of the ovaries, atrophy, hypertrophy, and metaplasia of the uterus, hyperplasia of the cervix, atrophy, hyperplasia, and mucification of the vagina, and estrous cycle variations at doses ≥3 mg/kg/day (≥12 times the exposure based on AUC in humans at the highest recommended dose). Adverse effects in male reproductive organs in rats included tubular degeneration and atrophy of the testes, degeneration of seminiferous tubules, cellular debris in the epididymides, epithelial atrophy and inflammation in the prostate, and atrophy in the seminal vesicles at doses ≥3 mg/kg/day (≥12 times the exposure based on AUC in humans at the highest recommended dose). Findings in the male rats were not reversible. In the 4-week repeat-dose toxicity studies in monkeys, oral administration of vorasidenib led to adverse effects in male and female reproductive organs including fibrotic hypoplasia of the testes in males at doses ≥10 mg/kg/day (approximately 17 times the exposure based on AUC in humans at the highest recommended dose) and decreased uterine weights in females at doses ≥10 mg/kg/day (approximately 22 times the exposure based on AUC in humans at the highest recommended dose). Findings in male and female monkeys were reversible.

13.2 Animal Toxicology and Pharmacology

In repeat-dose toxicity studies, oral administration of vorasidenib to rats for 28 days led to ototoxicity findings of reversible neutrophil infiltration of the epithelial lining of the middle ear and Eustachian tube at doses >3 mg/kg/day (>12-times the human exposure based on the AUC at the highest recommended dose). Additional findings in a 28-day ototoxicity study included edema in the tympanic cavity at doses >30 mg/kg/day. In addition, oral administration of vorasidenib to monkeys for 13 weeks resulted in dilated cardiomyopathy and secondary congestive heart failure at a dose of 20 mg/kg/day (105 times the human exposure based on the AUC at the highest recommended dose). Skeletal muscle was a target organ in the repeat dose toxicology studies in rats and monkeys at doses ≥13 times the AUC in patients at the highest recommended dose. Findings included decreased hind limb muscle tone, abnormal gait with limited hind limb usage, and low carriage, associated with small size and atrophy of the muscle in rats and necrosis and mononuclear/mixed cell infiltrates in the muscle in monkeys.

14 CLINICAL STUDIES

The efficacy of VORANIGO was evaluated in the INDIGO trial (Study AG881-C-004), a randomized, multicenter, double-blind, placebo-controlled study of 331 patients (NCT04164901). Eligible patients were required to have IDH1- or IDH2-mutant Grade 2 astrocytoma or oligodendroglioma with prior surgery including biopsy, sub-total resection, or gross total resection. Patients were required to have measurable, non-enhancing disease; patients with centrally confirmed minimal, non-nodular, non-measurable enhancement were eligible. Patients who received prior anti-cancer treatment, including chemotherapy or radiation therapy were excluded. Patients were randomized to receive either VORANIGO 40 mg orally once daily or placebo orally once daily until disease progression or unacceptable toxicity. IDH1 or IDH2 mutation status was prospectively determined by the Life Technologies Corporation Oncomine Dx Target Test.

Randomization was stratified by local 1p19q status (co-deleted or not co-deleted) and baseline tumor size (diameter ≥2 cm or <2 cm). Patients who were randomized to placebo were allowed to cross over to receive VORANIGO after documented radiographic disease progression. Tumor assessments were performed every 12 weeks.

A total of 331 patients were randomized, 168 to the VORANIGO arm and 163 to the placebo arm. The median age was 40 years (range: 16 to 71); 57% were male; 78% were White, 4% were Asian, 1% were Black or African American and 16% had race not reported; 78% were not Hispanic or Latino; 52% oligodendroglioma and 48% astrocytoma; 79% had one prior surgery and 21% had ≥2 prior surgeries. In the VORANIGO arm, 14% of patients had biopsy, 48% had sub-total resection and 51% had gross-total resection. The majority of IDH1 mutations consisted of R132H (87%). The other alleles were reported as follows: R132C (5%), R132G (3%), R132L (1%), and R132S (1%). IDH2 mutations consisted of R172K (2%) and R172G (1%).

The major efficacy outcome was progression-free survival (PFS) as evaluated by a blinded independent review committee (BIRC) per modified Response Assessment in Neuro-Oncology for Low Grade Glioma (RANO-LGG) criteria.

Efficacy results are summarized in Table 7 and Figure 1.

Table 7: Efficacy Results for the INDIGO Trial (Study AG881-C-004)
Efficacy Parameter | VORANIGO 40 mg daily (n=168) | Placebo (n=163)
Progression-Free Survival (PFS)
Number of Events, n (%)
Progressive disease | 47 (28) | 88 (54)
Death | 0 | 0
Hazard ratio (95% CI) [Stratified Cox proportional hazard model, stratified by 1p19q status and baseline tumor size.] | 0.39 (0.27, 0.56)
p-value [Based on one-sided stratified log-rank test compared to the pre-specified α of 0.000359 (one-sided).] | <0.0001
CI = Confidence Interval

Figure 1: Kaplan-Meier Curve for Progression-Free Survival per BIRC for the INDIGO Trial

The major efficacy analyses are supported by a prospectively defined key secondary outcome measure time to next intervention (defined as the time from randomization to the initiation of first subsequent anticancer therapy or death due to any cause). The median time to next intervention was not reached for patients in the VORANIGO arm and 17.8 months for patients in the placebo arm (HR=0.26; 95% CI: [0.15, 0.43], p <0.0001).

16 HOW SUPPLIED/STORAGE AND HANDLING

How Supplied

VORANIGO® (vorasidenib) tablets are supplied in two strengths:

10 mg tablets: White to off-white, round film-coated tablet imprinted with "10" in black ink on one side and plain on the other side.

- Each carton contains one 30-count bottle of 10 mg tablets with desiccant canister(s) and child-resistant cap (NDC 72694-879-10)

40 mg tablets: White to off-white, oblong film-coated tablet imprinted with "40" in black ink on one side and plain on the other side.

- Each carton contains one 30-count bottle of 40 mg tablets with desiccant canister(s) and child-resistant cap (NDC 72694-728-40)

Storage

Store at 20°C to 25°C (68°F to 77°F); excursions permitted between 15°C and 30°C (59°F to 86°F) [see USP Controlled Room Temperature].

17 PATIENT COUNSELING INFORMATION

Advise the patient to read the FDA-approved patient labeling (Patient Information).

Hepatotoxicity

Inform patients of the risk of hepatotoxicity and to promptly report any signs or symptoms of hepatotoxicity to their healthcare provider [see Warnings and Precautions (5.1)].

Embryo-Fetal Toxicity

Advise pregnant women and females of reproductive potential of the potential risk to a fetus. Advise females of reproductive potential to inform their healthcare provider of a known or suspected pregnancy [see Warnings and Precautions (5.2) and Use in Specific Populations (8.1, 8.3)].

Advise females of reproductive potential to use effective nonhormonal contraception during treatment with VORANIGO and for 3 months after the last dose [see Use in Specific Populations (8.3)] since VORANIGO can render some hormonal contraceptives ineffective [see Drug Interactions (7.2)].

Advise males with female partners of reproductive potential to use effective contraception during treatment with VORANIGO and for 3 months after the last dose [see Use in Specific Populations (8.3)].

Lactation

Advise women not to breastfeed during treatment with VORANIGO and for 2 months after the last dose [see Use in Specific Populations (8.2)].

Infertility

Advise females and males of reproductive potential that VORANIGO may impair fertility [see Use in Specific Populations (8.3) and Nonclinical Toxicology (13.1)].

Drug Interactions

Advise patients and caregivers to inform their healthcare provider of all concomitant medications, including prescription medicines, over-the counter drugs, vitamins and herbal products [see Drug Interactions (7)].

Advise patients and caregivers to inform their healthcare provider if they currently smoke tobacco as it may affect how well VORANIGO works [see Drug Interactions (7)].

Instructions for Taking VORANIGO

Advise patients to swallow tablets whole with a glass of water, with or without food, and to not split, crush or chew VORANIGO tablets [see Dosage and Administration (2.3)].

If a patient misses a dose by less than 6 hours, instruct patients to take the missed dose right away. If a patient misses a dose by 6 or more hours, instruct patients to skip the dose for that day. Advise patients to take the next dose at the usual time [see Dosage and Administration (2.3)].

If a patient vomits a dose, instruct patients not to take another dose. Advise patients to take the next dose at the usual time [see Dosage and Administration (2.3)].

Manufactured for Servier Pharmaceuticals LLC, Boston, MA 02210

Servier and the Servier logo are trademarks of Les Laboratoires Servier.

VORANIGO® is a registered trademark of Servier Pharmaceuticals LLC, a wholly owned, indirect subsidiary of Les Laboratoires Servier.

Oncomine™ Dx Target Test is a trademark of Life Sciences Corporation, a part of Thermo Fisher Scientific Inc.

© 2024 Servier Pharmaceuticals LLC

PATIENT INFORMATION
VORANIGO® (vo-rah-NEE-goh)
(vorasidenib)
tablets, for oral use

What is VORANIGO?
VORANIGO is a prescription medicine used to treat adults and children 12 years of age and older with certain types of brain tumors called astrocytoma or oligodendroglioma with an isocitrate dehydrogenase-1 (IDH1) or isocitrate dehydrogenase-2 (IDH2) mutation, following surgery.
Your healthcare provider will perform a test to make sure that VORANIGO is right for you.
It is not known if VORANIGO is safe and effective in children under 12 years of age.

Before taking VORANIGO, tell your healthcare provider about all of your medical conditions, including if you:

- have liver problems
- have kidney problems or are on dialysis
- smoke tobacco
- are pregnant or plan to become pregnant. VORANIGO can harm your unborn baby.
  Females who are able to become pregnant:
  - Your healthcare provider will do a pregnancy test before you start treatment with VORANIGO.
  - You should use effective nonhormonal birth control during treatment with VORANIGO and for 3 months after the last dose. VORANIGO may affect how hormonal contraceptives (birth control) work and cause them to not work well. Talk to your healthcare provider about birth control methods that may be right for you during treatment with VORANIGO.
  - Tell your healthcare provider right away if you become pregnant or think you may be pregnant during treatment with VORANIGO.
  Males with female partners who are able to become pregnant:
  - You should use effective birth control during treatment with VORANIGO and for 3 months after the last dose.
  - Tell your healthcare provider right away if your partner becomes pregnant or thinks she may be pregnant during your treatment with VORANIGO.

- are breastfeeding or plan to breastfeed. It is not known if VORANIGO passes into breast milk. Do not breastfeed during treatment with VORANIGO and for 2 months after the last dose.

Tell your healthcare provider about all the medicines you take, including prescription and over-the-counter medicines, vitamins and herbal supplements. VORANIGO may affect the way other medicines work and other medicines may affect how VORANIGO works.
Know the medicines you take. Keep a list of them to show your healthcare provider or pharmacist when you get a new medicine.

How should I take VORANIGO?

- Take VORANIGO exactly as your healthcare provider tells you.
- Do not change your dose or stop taking VORANIGO without talking to your healthcare provider.
- Take VORANIGO 1 time a day about the same time each day.
- Swallow VORANIGO tablets whole with water. Do not split, crush or chew the tablets.
- VORANIGO can be taken with or without food.
- If you miss a dose of VORANIGO by less than 6 hours, take the missed dose right away. If you miss a dose by more than 6 hours, skip the dose for that day. Take your next dose at your usual time.
- If you vomit after taking VORANIGO, do not take an extra dose. Take your next dose at your usual time.

What are the possible side effects of VORANIGO?
VORANIGO may cause serious side effects, including:

- Liver problems. Changes in liver function blood tests may happen during treatment with VORANIGO and can be serious. Your healthcare provider will do blood tests to check your liver function before and during treatment with VORANIGO. Tell your healthcare provider right away if you develop any of the following signs and symptoms of liver problems:
  - yellowing of your skin or the white part of your eyes (jaundice)
  - dark tea-colored urine
  - loss of appetite
  - pain on the upper right side of your stomach area
  - feeling very tired or weak

The most common side effects of VORANIGO include:

- increased liver enzyme levels in the blood
- lack of energy, tiredness
- headache
- COVID-19
- muscle aches or stiffness
- diarrhea
- nausea
- seizure

Your healthcare provider may change your dose, temporarily stop or permanently stop treatment with VORANIGO if you have certain side effects.
VORANIGO may affect fertility in females and males, which may affect the ability to have children. Talk to your healthcare provider if this is a concern for you.
These are not all of the possible side effects of VORANIGO.
Call your doctor for medical advice about side effects. You may report side effects to FDA at 1-800-FDA-1088.

How should I store VORANIGO?

- Store VORANIGO at room temperature between 68°F to 77°F (20°C to 25°C).
- VORANIGO comes with desiccant canisters (drying agent) in the bottle to help keep the medicine dry (protect from moisture). Do not remove the desiccant canisters from the bottle. Do not swallow the desiccant canisters.
- The VORANIGO bottle has a child resistant cap.

Keep VORANIGO and all medicines out of reach of children.

General information about the safe and effective use of VORANIGO.
Medicines are sometimes prescribed for purposes other than those listed in a Patient Information leaflet. Do not use VORANIGO for a condition for which it was not prescribed. Do not give VORANIGO to other people, even if they have the same symptoms that you have. It may harm them. You can ask your pharmacist or healthcare provider for information about VORANIGO that is written for health professionals.

What are the ingredients in VORANIGO?
Active ingredient: vorasidenib
Inactive ingredients: croscarmellose sodium, magnesium stearate, microcrystalline cellulose, silicified microcrystalline cellulose and sodium lauryl sulfate
Tablet coating: hypromellose, lactose monohydrate, macrogol and titanium dioxide
Black printing ink: black iron oxide, hypromellose and propylene glycol

Manufactured for Servier Pharmaceuticals LLC, Boston, MA 02210
Servier and the Servier logo are trademarks of Les Laboratoires Servier.
VORANIGO® is a registered trademark of Servier Pharmaceuticals LLC, a wholly owned, indirect subsidiary of Les Laboratoires Servier.
© 2024 Servier Pharmaceuticals LLC
For more information, go to www.VORANIGO.com or call 1-800-807-6124.

This Patient Information has been approved by the U.S. Food and Drug Administration.

Issued: 08/2024

PRINCIPAL DISPLAY PANEL - 10 mg Tablet Bottle Carton

NDC 72694-879-10

Voranigo®
(vorasidenib)
tablets

10 mg

Swallow tablets whole.
Do not split, crush, or chew the tablet.

1 bottle containing 30 tablets

Rx only

PRINCIPAL DISPLAY PANEL - 40 mg Tablet Bottle Carton

NDC 72694-728-40

Voranigo®
(vorasidenib)
tablets

40 mg

Swallow tablets whole.
Do not split, crush, or chew the tablet.

1 bottle containing 30 tablets

Rx only